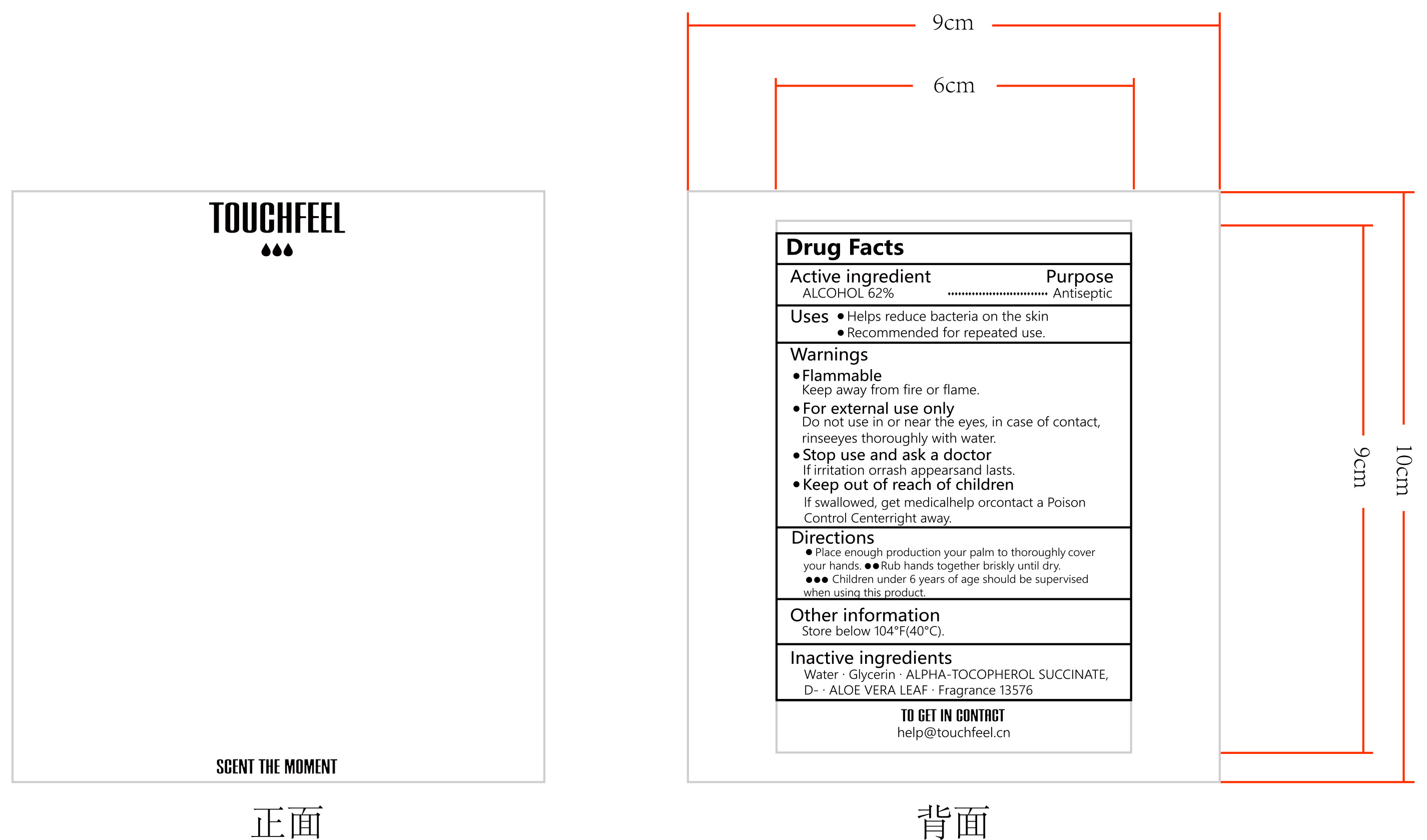 DRUG LABEL: HAND SANITIZER
NDC: 84778-072 | Form: PATCH
Manufacturer: Guangzhou Yixin Cross-border E-commerce Co., Ltd.
Category: otc | Type: HUMAN OTC DRUG LABEL
Date: 20250407

ACTIVE INGREDIENTS: ALCOHOL 1 mL/1 mL
INACTIVE INGREDIENTS: FRAGRANCE 13576; .ALPHA.-TOCOPHEROL SUCCINATE, D-; ALOE VERA LEAF; GLYCERIN; WATER

Active ingredients

ALCOHOL 62%

USES

Indications: This product is suitable for general skin disinfection and helps prevent the spread of diseases caused by bacteria.
Directions:
Before use, make sure your hands are dry.
Apply an appropriate amount of this product to the palm of your hand (about one teaspoon or press the nozzle 2-3 times), rub your hands thoroughly until it evaporates completely, no need to rinse with water.
Pay special attention to the cleaning of fingertips, around nails and thumbs.
It is recommended to wait for hands to dry naturally after each use before touching food or other items.
Precautions: Avoid contact with eyes. If contact occurs, rinse immediately with clean water. For external use only, avoid children using alone.

Purpose

Reduce or inhibit microbial growth, suitable for hand disinfection, helps reduce bacterial transmission

WARNINGS

Flammability: This product is a highly flammable liquid. Keep away from fire, sparks and hot surfaces. Do not use while smoking. Store in a cool, dry place away from direct sunlight.
Risk of ingestion: If swallowed, seek medical help or contact a poison control center immediately. This product is for external use only and is not suitable for oral use.
Skin sensitivity: If erythema, irritation or other allergic reactions occur during use, please stop use and consult a doctor. Avoid contact with eyes and broken skin. If accidentally contacted with eyes, rinse with plenty of water for at least 15 minutes and consult a doctor.
Children's use: It should be used under adult supervision. Avoid children from contacting and using this product alone to prevent accidental ingestion or abuse.
Precautions for long-term use: Long-term and frequent use may cause dryness, peeling or cracking of the skin. It is recommended to use with hand cream to keep the skin healthy.
Storage conditions: Store in the original packaging and keep away from children and unauthorized personnel. Make sure the container is well sealed to prevent leakage or evaporation.

DOSAGE AND ADMINISTRATION SECTION

Applicable people: Suitable for adults and children (adult supervision is recommended, especially for children under 6 years old).
How to use:
Apply an appropriate amount of hand sanitizer to the palm of your hand (about one teaspoon or press the nozzle 2-3 times), making sure to cover all surfaces of your hands.
Rub your hands thoroughly, including between your fingers, around your nails, and on your wrists, for at least 20 seconds until the liquid evaporates completely.
No need to rinse with water.
Dosage: Adjust the amount according to the size and degree of dirtiness of your hands, but 1-2 pumps (about 2-3 ml) are generally recommended for each use. It is important to ensure sufficient coverage to achieve the best disinfection effect.
Frequency: When soap and water are not available, especially at critical moments such as after contact with public facilities, after coughing or sneezing, and before and after handling food, frequent use should be used to maintain hand hygiene.
Precautions: Avoid contact with eyes and broken skin when using. If the above situation occurs, rinse immediately with clean water and consult a doctor. If any discomfort occurs, such as rash or allergic symptoms, stop using.

DO NOT USE SECTION

Contraindications: This product is for external use only. Oral administration is strictly prohibited. If swallowed, seek medical help or contact a poison control center immediately.

Allergic reactions: Do not use if you are allergic to any of the ingredients in this product. If rash, itching or other allergic symptoms occur, stop use and consult a doctor.

Use on broken skin: Avoid direct use on obvious wounds, abrasions or other forms of broken skin to prevent irritation or discomfort.

Eye use: Do not contact hand sanitizer with eyes. If it accidentally enters your eyes, rinse immediately with plenty of water for at least 15 minutes and seek medical help as needed.

High temperature environment storage: Do not store hand sanitizer in an extremely high temperature environment (for example, in direct sunlight such as in a car), as this may cause the container to swell or even rupture, and may affect the quality of the product.your hands or feet swell

scalp irritation or redness occurs

unwanted facial hair growth occurs

you do not see hair regrowth in 4 months

May be harmful if used when pregnant or breast-feeding.

Keep out of reach of children, lf swallowed, get medical help or contact a Poison Control Center right away.

WHEN USING SECTION

Avoid contact with eyes and mucous membranes: When using hand sanitizer, be careful not to let it come into contact with eyes, mouth or other mucous membranes. If contact occurs, rinse immediately with plenty of water and seek medical help as needed.
Keep away from fire and heat sources: Since most hand sanitizers contain flammable ingredients such as alcohol, please keep away from open flames, sparks and hot objects during use. Wait for hands to be completely dry after use before engaging in activities that may involve fire or heat sources.
Child supervision: When children use hand sanitizer, they must be supervised by an adult to prevent accidental ingestion or improper use. Teach children the correct method of use and explain its importance and safety.
Keep the container sealed and out of reach of children: After use, make sure the bottle cap is tightly closed to reduce evaporation and prevent accidental leakage. Store hand sanitizer where children cannot easily reach it to prevent accidental ingestion.
Use in moderation: Although using more hand sanitizer may seem to be cleaner, in fact, only the recommended dosage is needed to effectively disinfect hands. Excessive use is not only wasteful, but may also cause dryness or irritation of the skin.
Take care of your skin: Frequent use of hand sanitizer may cause dry skin. It is recommended to use moisturizer regularly to maintain skin health, especially in winter or if you have skin sensitivity.

STOP USE

Skin allergy or irritation: If you experience rash, redness, itching, swelling, pain or any other form of skin irritation during use of this product, please stop using it immediately and consult a doctor.
Handling after ingestion: This product is for external use only and is strictly prohibited for oral administration. If swallowed accidentally, please stop using it immediately and seek medical help or contact a poison control center.
Eye discomfort: If hand sanitizer accidentally comes into contact with your eyes and you still feel persistent discomfort or blurred vision after rinsing, please stop using it and seek medical attention as soon as possible.
Signs of infection: If there are open wounds or signs of infection on your hands (such as pus secretion, extreme redness and swelling, etc.), please avoid using hand sanitizer directly on the injured area and consult a professional medical staff.
Any other abnormal reactions: If the user has any unusual reaction to this product, including but not limited to systemic reactions such as difficulty breathing and dizziness, they should stop using it immediately and seek emergency medical help.

KEEP OUT OF REACH OF CHILDREN.

Storage location: Please place this product in a high place or locked in a safe place where children cannot reach it to prevent children from taking it by themselves.

Ingestion treatment: If a child accidentally swallows the hand sanitizer, please stop using it immediately and seek medical help or contact the poison control center. Even if there are no symptoms of discomfort, you should consult a professional.

Educate children to use it correctly: Educate children that hand sanitizer is only used for hand cleaning and disinfection, not food or toys, and should be used under adult supervision.

Emergency contact information: In the event of any accident, please prepare the contact number of the local poison control center or other emergency contact information to get help quickly.

INACTIVE INGREDIENT

Water

Glycerin

.ALPHA.-TOCOPHEROL SUCCINATE, D-

ALOE VERA LEAF
Fragrance 13576